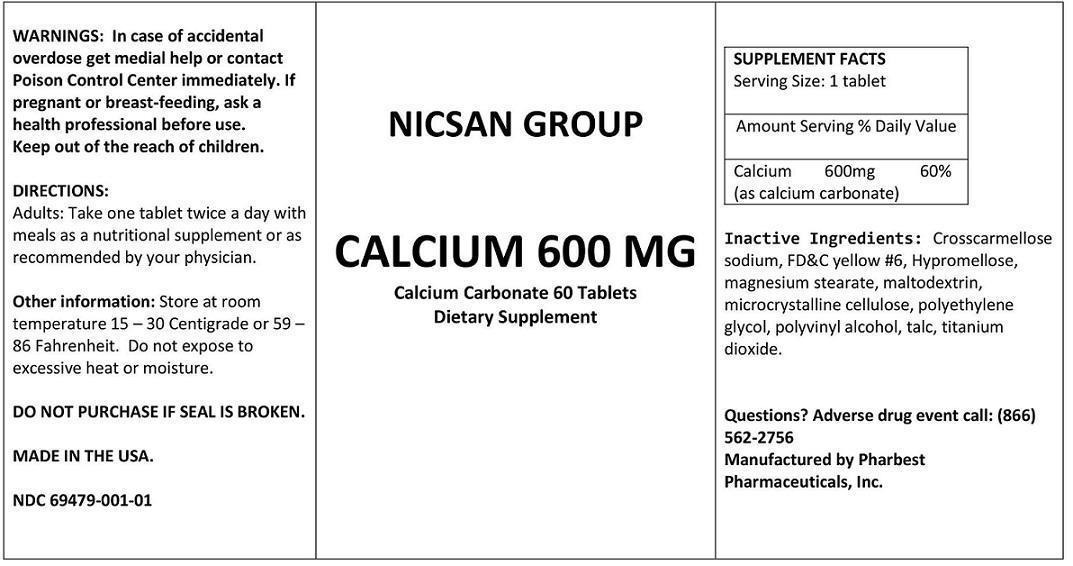 DRUG LABEL: CALCIUM 600 MG
NDC: 69479-001 | Form: TABLET
Manufacturer: NICSAN GROUP INC
Category: other | Type: DIETARY SUPPLEMENT
Date: 20151109

ACTIVE INGREDIENTS: CALCIUM CARBONATE 600 mg/1 1
INACTIVE INGREDIENTS: CROSCARMELLOSE SODIUM; FD&C YELLOW NO. 6; HYPROMELLOSES; MAGNESIUM STEARATE; MALTODEXTRIN; CELLULOSE, MICROCRYSTALLINE; POLYETHYLENE GLYCOLS; POLYVINYL ALCOHOL; TALC; TITANIUM DIOXIDE

CALCIUM 600 MG

STATEMENT OF IDENTITY

SUPPLEMENT FACTS Serving Size: 1 tablet
 | Amount Serving | % Daily Value
Calcium; (as calcium carbonate) | 600mg | 60%

Inactive Ingredients: Crosscarmellose sodium, FD&C yellow #6, Hypromellose, magnesium stearate,

maltodextrin, microcrystalline cellulose, polyethylene glycol, polyvinyl alcohol, talc, titanium dioxide.

WARNINGS

WARNINGS: In case of accidental overdose get medial help or contact Poison Control Center immediately.

If pregnant or breast-feeding, ask a health professional before use.

Keep out of the reach of children.

PRECAUTIONS

DO NOT PURCHASE IF SEAL IS BROKEN.

Other information: Store at room temperature 15 – 30 Centigrade or 59 – 86 Fahrenheit. Do not expose to excessive heat or moisture.

Questions? Adverse drug event call:(866) 562-2756

DIRECTIONS:

Adults: Take one tablet twice a day with meals as a nutritional supplement or as recommended by your physician.

HEALTH CLAIM

Calcium Carbonate 60 Tablets
Dietary Supplement